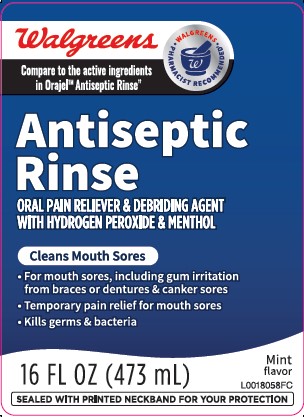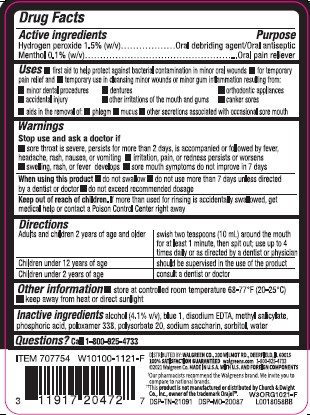 DRUG LABEL: Oral Sore Antiseptic
NDC: 0363-1045 | Form: LIQUID
Manufacturer: Walgreen Co.
Category: otc | Type: HUMAN OTC DRUG LABEL
Date: 20260212

ACTIVE INGREDIENTS: HYDROGEN PEROXIDE 1.5 mg/1 mL; MENTHOL 1 mg/1 mL
INACTIVE INGREDIENTS: FD&C BLUE NO. 1; EDETATE DISODIUM ANHYDROUS; METHYL SALICYLATE; PHOSPHORIC ACID; POLOXAMER 338; POLYSORBATE 20; SACCHARIN SODIUM; SORBITOL; WATER; ALCOHOL

Walgreens 024.000/024AA-AB
Oral Sore Antiseptic Rinse

active ingredients

Hydrogen peroxide 1.5% (w/v)

Menthol 0.1% (w/v)

purpose

Oral debriding agent/Oral antiseptic
Oral pain reliever

uses

- first aid to help protect against bacterial contamination in minor oral wounds
- for temporary pain relief and
- temporary use in cleansing minor wounds or minor gum inflammation resulting from:
- minor dental procedures
- dentures
- orthodontic appliances
- accidental injury
- other irritations of the mouth and gums
- canker sores
- aids in the removal of:
- phlegm
- mucus
- other secretions associated with occasional sore mouthUses

Warnings

for this product

Stop use and ask a doctor if

- sore throat is severe, persists for more than 2 days, is accompanied or followed by fever, headache, rash, nausea, or vomiting
- irritation, pain, or redness persists or worsens
- swelling, rash, or fever develops
- sore mouth symptoms do not improve in 7 days

When using this product

- do not swallow
- do not use more than 7 days unless directed by a dentist or doctor
- do not exceed recommended dosage

Keep out of reach of children.

If more than used for rinsing is accidentally swallowed, get medical help or contact a Poison Control Center right away.

directions

Adults and children 2 years of age and older - swish two teaspoons (10 mL) around the mouth for at least 1 minute, then spit out; use up to 4 times daily or as directed by a dentist or physician

Children under 12 years of age - should be supervised in the use of the product

Children under 2 years of age - consult a dentist or doctor

other information

- store at controlled room temperature 68-77°F (20-25°C)
- keep away from heat or direct sunlight

inactive ingredients

alcohol (4.1% v/v), blue 1, disodium EDTA, methyl salicylate, phosphoric acid, poloxamer 338, polysorbate 20, sodium saccharin, sorbitol, water

Questions?

Call 1-800-925-4733

ADVERSE REACTION

DISTRIBUTED BY: WALGREEN CO., 200 WILMOT RD., DEERFIELD, IL 60015

100% SATISFACTION GUARANTEED walgreens.com 1-800-925-4733

©2021 Walgreen Co. MADE IN U.S.A. WITH U.S. AND FOREIGN COMPONENTS

†Our pharmacists recommend the Walgreens brand. We invite you to compare to national brands.

‡This product is not manufactured or distributed by Church & Dwight Co., Inc owner of the trademark Orajel™.

DSP-TN-21091 DSP-MO-20087

Principal display panel

Walgreens

WALGREENS - PHARMACIST RECOMMENDED

Compare to the active ingredients in Orajel™ Antiseptic Rinse‡

Antiseptic

Rinse

ORAL PAIN RELIEVER & DEBRIDING AGENT WITH HYDROGEN PEROXIDE & MENTHOL

Cleans Mouth Sores

- For mouth sores, including gum irritation from braces or dentures & canker sores
- Temporary pain relief for mouth sores
- Kills germs & bacterial

Mint flavor

16 FL OZ (473 mL)

SEALED WITH PRINTED NECKBAND FOR YOUR PROTECTION